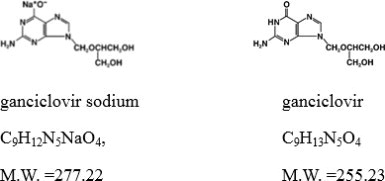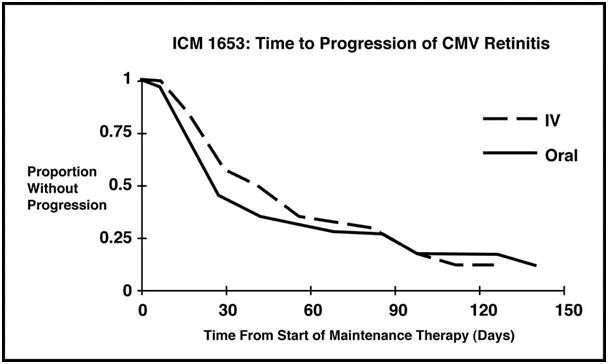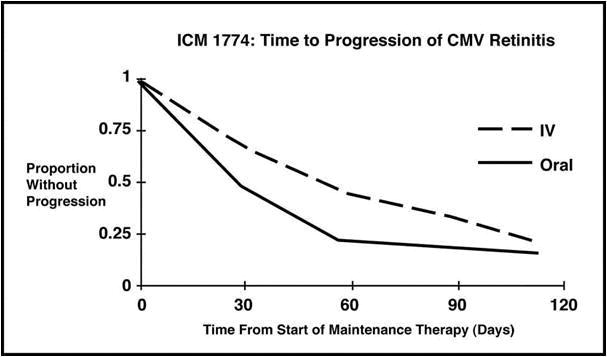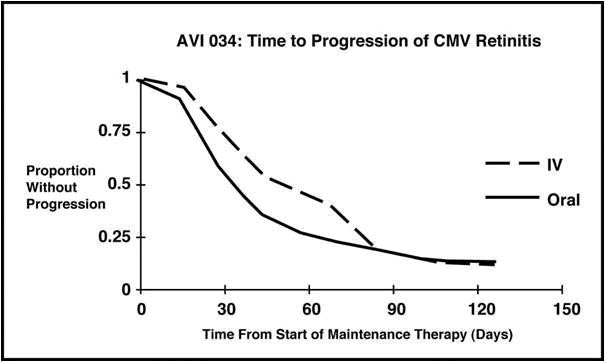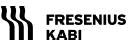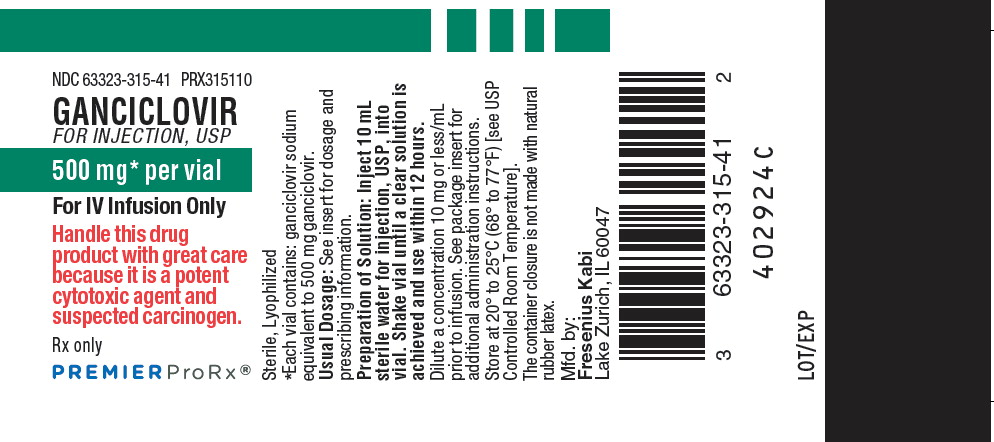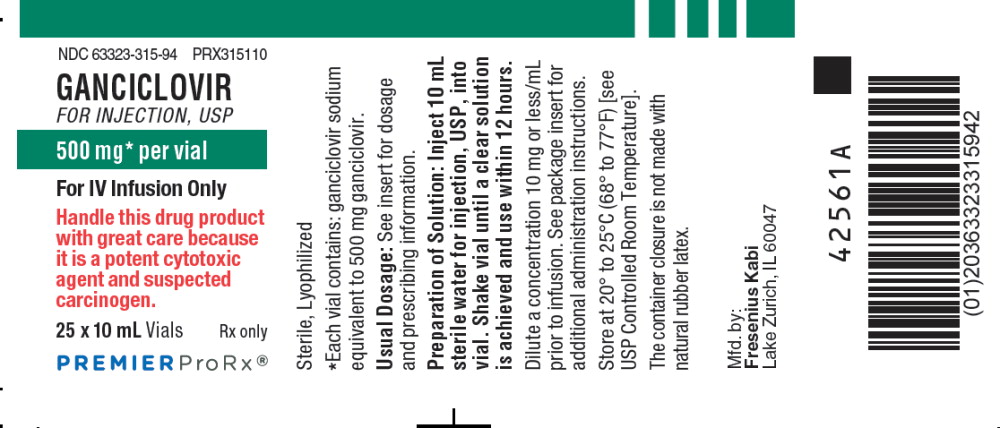 DRUG LABEL: Ganciclovir
NDC: 63323-315 | Form: INJECTION, POWDER, LYOPHILIZED, FOR SOLUTION
Manufacturer: Fresenius Kabi USA, LLC
Category: prescription | Type: HUMAN PRESCRIPTION DRUG LABEL
Date: 20260109

ACTIVE INGREDIENTS: GANCICLOVIR SODIUM 500 mg/10 mL
INACTIVE INGREDIENTS: Hydrochloric Acid; Sodium Hydroxide

HIGHLIGHTS OF PRESCRIBING INFORMATION

These highlights do not include all the information needed to use GANCICLOVIR FOR INJECTION safely and effectively. See full prescribing information for GANCICLOVIR FOR INJECTION.
GANCICLOVIR FOR INJECTION, for intravenous use
Initial U.S. Approval: 1989
Rx only

WARNING: HEMATOLOGIC TOXICITY, IMPAIRMENT OF FERTILITY, FETAL TOXICITY, MUTAGENESIS AND CARCINOGENESIS

See full prescribing information for complete boxed warning.

- Hematologic Toxicity: Granulocytopenia, anemia, thrombocytopenia, and pancytopenia have been reported in patients treated with Ganciclovir for Injection. (5.1)
- Impairment of Fertility: Based on animal data and limited human data, Ganciclovir for Injection may cause temporary or permanent inhibition of spermatogenesis in males and suppression of fertility in females. (5.3)
- Fetal Toxicity: Based on animal data, Ganciclovir for Injection has the potential to cause birth defects in humans. (5.4)
- Mutagenesis and Carcinogenesis: Based on animal data, Ganciclovir for Injection has the potential to cause cancer in humans. (5.5)

1 INDICATIONS AND USAGE

Ganciclovir for Injection is a deoxynucleoside analogue cytomegalovirus (CMV) DNA polymerase inhibitor indicated for the:

- treatment of CMV retinitis in immunocompromised adult patients, including patients with acquired immunodeficiency syndrome (AIDS). (1.1)
- prevention of CMV disease in adult transplant recipients at risk for CMV disease. (1.2)

2 DOSAGE AND ADMINISTRATION

- Ganciclovir for Injection is administered only intravenously. (2.1)

Dosage in Adult Patients with Normal Renal Function

Treatment of CMV retinitis (2.3)

Induction: 5 mg/kg (given intravenously at a constant rate over 1 hour) every 12 hours for 14 to 21 days.

Maintenance: 5 mg/kg (given intravenously at a constant rate over 1 hour) once daily for 7 days per week, or 6 mg/kg once daily for 5 days per week.

Prevention of CMV disease in transplant recipients (2.4)

Induction: 5 mg/kg (given intravenously at a constant rate over 1 hour) every 12 hours for 7 to 14 days.

Maintenance: 5 mg/kg (given intravenously at a constant rate over 1 hour) once daily, 7 days per week, or 6 mg/kg once daily, 5 days per week until 100 to 120 days post-transplantation.

Adults with renal impairment: Adjust dosage based on creatinine clearance. (2.5)

3 DOSAGE FORMS AND STRENGTHS

- For injection: 500 mg of ganciclovir as lyophilized powder in a single-dose vial for reconstitution. (3)

4 CONTRAINDICATIONS

- Hypersensitivity to ganciclovir or valganciclovir. (4)

5 WARNINGS AND PRECAUTIONS

- Renal Impairment: Increased serum creatinine levels have been observed with the use of Ganciclovir for Injection, particularly in elderly patients and transplant recipients receiving concomitant nephrotoxic drugs. Monitor renal function during therapy with Ganciclovir for Injection, particularly in elderly patients and in patients taking other nephrotoxic drugs, and reduce dosage in patients with renal impairment. (5.2)

6 ADVERSE REACTIONS

Most common adverse reactions and laboratory abnormalities reported in at least 20% of patients were: pyrexia, diarrhea, leukopenia, nausea, anemia, asthenia, headache, cough, decreased appetite, dyspnea, abdominal pain, sepsis, hyperhidrosis, and blood creatinine increased. (6.1)

To report SUSPECTED ADVERSE REACTIONS, contact Fresenius Kabi USA, LLC at 1-800-5517176 or FDA at 1-800-FDA-1088 or www.fda.gov/medwatch.

7 DRUG INTERACTIONS

- Imipenem-cilastatin: Seizures were reported in patients receiving ganciclovir and imipenem-cilastatin.
- Concomitant use is not recommended unless the potential benefits outweigh the risks. (7)
- Cyclosporine or amphotericin B: When coadministered with ganciclovir, the risk of nephrotoxicity may be increased. Monitor renal function. (5.2, 7)
- Mycophenolate mofetil (MMF): When coadministered with ganciclovir, the risk of hematological and renal toxicity may be increased. Monitor for ganciclovir and MMF toxicity. (7)
- Other drugs associated with myelosuppression or nephrotoxicity: Due to potential for increased toxicity, such drugs should be considered for concomitant use with ganciclovir only if the potential benefits are judged to outweigh the risks. (7)
- Didanosine: Ganciclovir coadministered with didanosine may increase didanosine levels. Monitor for didanosine toxicity (e.g., pancreatitis). (7)
- Probenecid: May increase ganciclovir levels. Monitor for evidence of ganciclovir toxicity. (7)

8 USE IN SPECIFIC POPULATIONS

- Lactation: Breastfeeding is not recommended with use of Ganciclovir for Injection. (8.2)

FULL PRESCRIBING INFORMATION

WARNING: HEMATOLOGIC TOXICITY, IMPAIRMENT OF FERTILITY, FETAL TOXICITY, MUTAGENESIS AND CARCINOGENESIS

- Hematologic Toxicity: Granulocytopenia, anemia, thrombocytopenia, and pancytopenia have been reported in patients treated with Ganciclovir for Injection [see Warnings and Precautions (5.1)].
- Impairment of Fertility: Based on animal data and limited human data, Ganciclovir for Injection may cause temporary or permanent inhibition of spermatogenesis in males and suppression of fertility in females [see Warnings and Precautions (5.3)].
- Fetal Toxicity: Based on animal data, Ganciclovir for Injection has the potential to cause birth defects in humans [see Warnings and Precautions (5.4)].
- Mutagenesis and Carcinogenesis: Based on animal data, Ganciclovir for Injection has the potential to cause cancers in humans [see Warnings and Precautions (5.5)].

1 INDICATIONS AND USAGE

1.1 Treatment of CMV Retinitis

Ganciclovir for Injection is indicated for the treatment of cytomegalovirus (CMV) retinitis in immunocompromised adult patients, including patients with acquired immunodeficiency syndrome (AIDS) [see Clinical Studies (14.1)].

1.2 Prevention of CMV Disease in Transplant Recipients

Ganciclovir for Injection is indicated for the prevention of CMV disease in adult transplant recipients at risk for CMV disease [see Clinical Studies (14.2)].

2 DOSAGE AND ADMINISTRATION

2.1 Important Dosing and Administration Information

- To avoid phlebitis/pain at the infusion site, Ganciclovir for Injection must only be administered by intravenous infusion over 1 hour, preferably via plastic cannula, into a vein with adequate blood flow to permit rapid dilution and distribution.
- Do not administer Ganciclovir for Injection by rapid or bolus intravenous injection which may increase toxicity as a result of excessive plasma levels.
- The recommended dosage and infusion rate for Ganciclovir for Injection should not be exceeded.
- Do not administer the reconstituted Ganciclovir for Injection solution intramuscularly or subcutaneously because it may result in severe tissue irritation due to high pH [see Description 11].
- Administration of Ganciclovir for Injection should be accompanied by adequate hydration.
- Parenteral drug products should be inspected visually for particulate matter and discoloration prior to administration, whenever solution and container permit.

2.2 Testing Before and During Treatment

- Females of reproductive potential should undergo pregnancy testing before initiation of treatment with Ganciclovir [see Warnings and Precautions (5.4), Use in Specific Populations (8.1, 8.3)].
- Complete blood counts with differential and platelet counts should be performed frequently, especially in patients in whom Ganciclovir for Injection or other nucleoside analogues have previously resulted in cytopenias, or in whom absolute neutrophil counts are less than 1000 cells/μL at the beginning of treatment [see Warnings and Precautions (5.1)].
- All patients should be monitored for renal function before and during treatment with Ganciclovir for Injection and dose should be adjusted as needed [see Dosage and Administration (2.5), Warnings and Precautions (5.2)].
- Patients with CMV retinitis should have frequent ophthalmological examinations during treatment with Ganciclovir for Injection solution to monitor disease status and for other retinal abnormalities [see Adverse Reactions (6.1)].

2.3 Recommended Dosage for Treatment of CMV Retinitis in Adult Patients with Normal Renal Function

Induction Dosage: The recommended initial dosage of Ganciclovir for Injection for patients with normal renal function is 5 mg/kg (given intravenously at a constant rate over 1 hour) every 12 hours for 14 to 21 days.

Maintenance Dosage: Following induction treatment, the recommended maintenance dosage of Ganciclovir for Injection is 5 mg/kg (given intravenously at a constant rate over 1 hour) once daily for 7 days per week, or 6 mg/kg once daily for 5 days per week.

2.4 Recommended Dosage for the Prevention of CMV Disease in Adult Transplant Recipients with Normal Renal Function

Induction Dosage: The recommended initial dosage of Ganciclovir for Injection for patients with normal renal function is 5 mg/kg (given intravenously at a constant rate over 1 hour) every 12 hours for 7 to 14 days.

Maintenance Dosage: Following induction, the recommended maintenance dosage of Ganciclovir for Injection is 5 mg/kg (given intravenously at a constant rate over 1 hour) once daily for 7 days per week, or 6 mg/kg once daily for 5 days per week until 100 to 120 days post-transplantation.

2.5 Recommended Dosage in Adult Patients with Renal Impairment

For patients with impairment of renal function, refer to Table 1 for recommended doses of Ganciclovir for Injection for induction and maintenance dosage for treatment of CMV retinitis and prevention of CMV disease in transplant recipients. Carefully monitor serum creatinine or creatinine clearance before and during treatment to allow for dosage adjustments in patients with impaired renal function.

Table 1. Recommended Induction and Maintenance Dosage for Adult Patients with Renal Impairment
Creatinine Clearance* (mL/min) | GANCICLOVIR Induction Dose (mg/kg) | Dosing Interval (hours) for Induction | Ganciclovir Maintenance Dose (mg/kg) | Dosing Interval (hours) for Maintenance
Greater than or equal to 70 | 5 | 12 | 5 | 24
50-69 | 2.5 | 12 | 2.5 | 24
25-49 | 2.5 | 24 | 1.25 | 24
10-24 | 1.25 | 24 | 0.625 | 24
Less than 10 | 1.25 | 3 times per week, following hemodialysis | 0.625 | 3 times per week, following hemodialysis
* Creatinine clearance can be related to serum creatinine by the formulas given below.

Creatinine clearance for males =

(140 - age [yrs]) (body wt [kg])

(72) (serum creatinine [mg/dL])

Creatinine clearance for females = 0.85 × male value

Patients Undergoing Hemodialysis

Induction dosing for Ganciclovir for Injection in patients undergoing hemodialysis should not exceed 1.25 mg/kg 3 times per week; and maintenance dosing should not exceed 0.625 mg/kg 3 times per week following each hemodialysis session. Ganciclovir for Injection should be given shortly after completion of the hemodialysis session, since hemodialysis has been shown to reduce plasma levels by approximately 50% [see Clinical Pharmacology (12.3)].

2.6 Preparation of Ganciclovir for Injection

Ganciclovir for Injection must be reconstituted and diluted under the supervision of a healthcare provider and administered as intravenous infusion. Each 10 mL clear glass vial contains 543 mg ganciclovir sodium equivalent to 500 mg of ganciclovir. Wearing disposable gloves is recommended during reconstitution and when wiping the outer surface of the vial and the table after reconstitution.

The contents of the vial should be prepared for administration in the following manner:

1. Reconstitution Instructions:
  a) Reconstitute lyophilized Ganciclovir for Injection by injecting 10 mL of sterile water for injection, USP, into the vial. Do not use bacteriostatic water for injection containing parabens. It is incompatible with Ganciclovir for Injection and may cause precipitation.
  b) Gently swirl the vial in order to ensure complete wetting of the product. Continue swirling until a clear reconstituted solution is obtained.
  c) Visually inspect the reconstituted solution for particulate matter and discoloration prior to proceeding with infusion. Discard the vial if particulate matter or discoloration is observed.
  d) Reconstituted solution in the vial is stable at room temperature (25°C (77°F)) for 12 hours. Do not refrigerate or freeze. Discard any unused portion of the reconstituted solution.
2. Infusion Instructions:
  a) Based on patient weight, the appropriate volume of the reconstituted solution (ganciclovir concentration 50 mg/mL) should be removed from the vial and added to an acceptable infusion fluid (typically 100 mL) for delivery over the course of 1 hour. Infusion concentrations greater than 10 mg/mL are not recommended. The following infusion fluids have been determined to be chemically and physically compatible with Ganciclovir for Injection solution: 0.9% Sodium Chloride, 5% Dextrose, Ringer's Injection and Lactated Ringer's Injection, USP.
  b) Ganciclovir for Injection, when reconstituted with sterile water for injection (nonbacteriostatic) and further diluted with 0.9% sodium chloride injection or other acceptable infusion fluid as specified above, should be used within 24 hours of dilution to reduce the risk of bacterial contamination. The diluted infusion solution should be refrigerated (2°C to 8 °C (36° to 46°F)). Do not freeze.

2.7 Handling and Disposal

Caution should be exercised in the handling and preparation of solutions of Ganciclovir for Injection. Solutions of Ganciclovir for Injection are alkaline (pH 11). Avoid direct contact of the skin or mucous membranes with Ganciclovir for Injection solution. If such contact occurs, wash thoroughly with soap and water; rinse eyes thoroughly with plain water. Wearing disposable gloves is recommended.

Because ganciclovir shares some of the properties of antitumor agents (i.e., carcinogenicity and mutagenicity), consideration should be given to handling and disposal according to guidelines issued for antineoplastic drugs.^1 Discard any unused portion of the reconstituted solution [see How Supplied/Storage and Handling (16)].

3 DOSAGE FORMS AND STRENGTHS

For injection: Single-dose vial containing 500 mg of ganciclovir as a sterile lyophilized white to off-white powder for reconstitution with 10 mL of preservative-free sterile water for injection, USP for intravenous use. The concentration of ganciclovir in the reconstituted solution is 50 mg/mL [see Dosage and Administration (2.6)].

4 CONTRAINDICATIONS

Ganciclovir for Injection is contraindicated in patients who have experienced a clinically significant hypersensitivity reaction (e.g., anaphylaxis) to ganciclovir, valganciclovir, or any component of the formulation.

5 WARNINGS AND PRECAUTIONS

5.1 Hematologic Toxicity

Granulocytopenia (neutropenia), anemia, thrombocytopenia and pancytopenia have been observed in patients treated with Ganciclovir for Injection. The frequency and severity of these events vary widely in different patient populations [see Adverse Reactions (6.1)]. Ganciclovir for Injection is not recommended if the absolute neutrophil count is less than 500 cells/μL, hemoglobin is less than 8 g/dL, or the platelet count is less than 25,000 cells/μL. Ganciclovir for Injection should also be used with caution in patients with pre-existing cytopenias and in patients receiving myelosuppressive drugs or irradiation. Granulocytopenia (neutropenia) usually occurs during the first or second week of treatment but may occur at any time during treatment. Cell counts usually begin to recover within 3 to 7 days after discontinuing drug. Colony-stimulating factors have been shown to increase neutrophil and white blood cell counts in patients receiving Ganciclovir for Injection solution for treatment of CMV retinitis.

Due to the frequency of neutropenia, anemia and thrombocytopenia in patients receiving Ganciclovir for Injection [see Adverse Reactions (6.1)], complete blood counts with differential and platelet counts should be performed frequently in all patients, especially in patients with renal impairment and in patients in whom ganciclovir or other nucleoside analogues have previously resulted in leukopenia, or in whom neutrophil counts are less than 1000 cells/μL at the beginning of treatment [see Dosage and Administration (2.2)].

5.2 Renal Impairment

Ganciclovir for Injection should be used with caution in patients with impaired renal function because the half-life and plasma/serum concentrations of ganciclovir will be increased due to reduced renal clearance. If renal function is impaired, dosage adjustments are recommended [see Dosage and Administration (2.5), Use in Specific Populations (8.5, 8.6)].

Increased serum creatinine levels have been reported in elderly patients and in transplant recipients receiving concomitant nephrotoxic medications (i.e., cyclosporine and amphotericin B). Monitoring renal function during therapy with Ganciclovir for Injection is essential, especially for elderly patients and those patients receiving concomitant agents that may cause nephrotoxicity [see Dosage and Administration (2.5), Drug Interactions (7), Use in Specific Populations (8.5)].

5.3 Impairment of Fertility

Based on animal data and limited human data, Ganciclovir for Injection at the recommended human dose (RHD) may cause temporary or permanent inhibition of spermatogenesis in males, and may cause suppression of fertility in females. Advise patients that fertility may be impaired with the use of Ganciclovir for Injection [see Use in Specific Populations (8.1, 8.3), Nonclinical Toxicology (13.1)].

5.4 Fetal Toxicity

Ganciclovir for Injection may cause fetal toxicity when administered to pregnant women based on findings in animal studies. Systemic exposure of ganciclovir in animals at approximately 2 times the RHD caused fetal growth retardation, embryolethality, teratogenicity, and/or maternal toxicity. Teratogenic changes in animals included cleft palate, anophthalmia/microphthalmia, aplastic organs (kidney and pancreas), hydrocephaly and brachygnathia. Women of childbearing potential should be advised to use effective contraception during treatment and for at least 30 days following treatment with Ganciclovir for Injection. Similarly, men should be advised to practice barrier contraception during and for at least 90 days following treatment with Ganciclovir for Injection [see Use in Specific Populations (8.1, 8.3), Nonclinical Toxicology (13.1)].

5.5 Mutagenesis and Carcinogenesis

Animal data indicate that ganciclovir is mutagenic and carcinogenic. Ganciclovir for Injection should therefore be considered a potential carcinogen in humans [see Dosage and Administration (2.7), Nonclinical Toxicology (13.1)].

6 ADVERSE REACTIONS

The following serious adverse reactions are discussed in greater detail in other sections of the labeling:

- Hematologic Toxicity [see Warnings and Precautions (5.1)]
- Renal Impairment [see Warnings and Precautions (5.2)]
- Impairment of Fertility [see Warnings and Precautions (5.3)]
- Fetal Toxicity [see Warnings and Precautions (5.4)]
- Mutagenesis and Carcinogenesis [see Warnings and Precautions (5.5)]

6.1 Clinical Trials Experience in Adult Patients

Because clinical trials are conducted under widely varying conditions, adverse reaction rates observed in the clinical trials of a drug cannot be directly compared to rates in the clinical trials of another drug and may not reflect rates observed in practice. The most common adverse reactions and laboratory abnormalities reported in at least 20% of patients were pyrexia, diarrhea, leukopenia, nausea, anemia, asthenia, headache, cough, decreased appetite, dyspnea, abdominal pain, sepsis, hyperhidrosis, and blood creatinine increased.

Selected adverse reactions that occurred during clinical trials of Ganciclovir for Injection are summarized below, according to the participating study patient population.

Adverse Reactions in Patients with CMV Retinitis: Three controlled, randomized, phase 3 trials comparing Ganciclovir for Injection and ganciclovir capsules for maintenance treatment of CMV retinitis have been completed. During these trials, Ganciclovir for Injection or ganciclovir capsules were prematurely discontinued in 9% of subjects because of adverse reactions. Selected adverse reactions and laboratory abnormalities reported during the conduct of these controlled trials are summarized in Table 2 and Table 3, respectively [see Clinical Studies (14.1)].

Table 2. Pooled Selected Adverse Reactions Reported in ≥ 5% of Subjects Comparing Ganciclovir for Injection to Ganciclovir Capsules for Maintenance Treatment of CMV Retinitis
Adverse Reaction |  | Maintenance Treatment Studies
Adverse Reaction |  | Ganciclovir for Injection (n=179) | Ganciclovir Capsules (n=326)
Pyrexia |  | 48% | 38%
Diarrhea |  | 44% | 41%
Leukopenia |  | 41% | 29%
Anemia |  | 25% | 19%
Total catheter events |  | 22% | 6%
 | Catheter infection | 9% | 4%
 | Catheter sepsis | 8% | 1%
 | Other catheter related events | 5% | 1%
Sepsis |  | 15% | 4%
Decreased appetite |  | 14% | 15%
Vomiting |  | 13% | 13%
Infection |  | 13% | 9%
Hyperhidrosis |  | 12% | 11%
Chills |  | 10% | 7%
Neuropathy peripheral |  | 9% | 8%
Thrombocytopenia |  | 6% | 6%
Pruritus |  | 5% | 6%

Retinal Detachment: Retinal detachment has been observed in subjects with CMV retinitis both before and after initiation of therapy with ganciclovir. Its relationship to therapy with ganciclovir is unknown. Retinal detachment occurred in 11% of patients treated with Ganciclovir for Injection and in 8% of patients treated with ganciclovir capsules.

Table 3. Selected Laboratory Abnormalities in Trials for Treatment of CMV Retinitis
Laboratory Abnormalities | CMV Retinitis Treatment*
Laboratory Abnormalities | Ganciclovir for Injection† 5 mg/kg/day (N=175) % | Ganciclovir Capsules‡ 3000 mg/day (N=320) %
Neutropenia with Absolute Neutrophil Count (ANC) per μL:
<500 | 25 | 18
500-<749 | 14 | 17
750-<1000 | 26 | 19
Anemia with Hemoglobin (g/dL):
<6.5 g/dL | 5 | 2
6.5-<8.0 | 16 | 10
8.0-<9.5 | 26 | 25
Serum Creatinine (mg/dL):
≥2.5 | 2 | 1
≥1.5 - <2.5 | 14 | 12
* Pooled data from Treatment Studies: ICM 1653, ICM 1774 and AVI 034
Mean time on therapy = 103 days, including allowed re-induction treatment periods
Mean time on therapy = 91 days, including allowed re-induction treatment periods

Adverse Reactions in Transplant Recipients: There have been three controlled clinical trials of Ganciclovir for Injection for the prevention of CMV disease in transplant recipients. Selected laboratory abnormalities are summarized in Table 4 and Table 5 below. Table 4 shows the frequency of neutropenia and thrombocytopenia and Table 5 shows the frequency of elevated serum creatinine values observed in these trials [see Clinical Studies (14.2)].

Table 4. Laboratory Abnormalities in Controlled Trials-Transplant Recipients who Received Ganciclovir for Injection, Placebo, or Control
Ganciclovir for Injection
 | Heart Allograft* |  | Bone Marrow Allograft†
 | Ganciclovir for Injection (n=76) | Placebo (n=73) | Ganciclovir for Injection (n=57) | Control (n=55)
Neutropenia
Absolute Neutrophil Count (ANC) per μL
<500 | 4% | 3% | 12% | 6%
500-1000 | 3% | 8% | 29% | 17%
Total ANC
≤1000/μL | 7% | 11% | 41% | 23%
Thrombocytopenia
Platelet count per μL
<25,000 | 3% | 1% | 32% | 28%
25,000-50,000 | 5% | 3% | 25% | 37%
Total Platelet Count
≤50,000/μL | 8% | 4% | 57% | 65%
* Study ICM 1496. Mean duration of treatment = 28 days
† Study ICM 1570 and ICM 1689. Mean duration of treatment = 45 days

Table 5. Serum Creatinine Levels in Controlled Trials-Transplant Recipients who Received Ganciclovir for Injection or Placebo
Serum Creatinine Levels (mg/dL) | Heart Allograft ICM 1496 |  | Bone Marrow Allograft ICM 1570 |  | Bone Marrow Allograft ICM 1689
Serum Creatinine Levels (mg/dL) | Ganciclovir for Injection (n=76) | Placebo (n=73) | Ganciclovir for Injection (n=20) | Control (n=20) | Ganciclovir for Injection (n=37) | Placebo (n=35)
≥2.5 mg/dL | 18% | 4% | 20% | 0% | 0% | 0%
≥1.5 - <2.5 | 58% | 69% | 50% | 35% | 43% | 44%

Other Adverse Reactions in Clinical Trials in Patients with CMV Retinitis and in Transplant Recipients

Adverse drug reactions with Ganciclovir for Injection or ganciclovir capsules in controlled clinical studies in either subjects with AIDS or transplant recipients are listed below [see Clinical Studies (14)]. All these events occurred in at least 3 subjects.

Blood and lymphatic disorders: pancytopenia, bone marrow failure

Cardiac disorders: arrhythmia

Ear and labyrinth disorders: tinnitus, ear pain, deafness

Eye disorders: visual impairment, vitreous disorders, eye pain, conjunctivitis, macular edema

Gastrointestinal disorders: nausea, abdominal pain, dyspepsia, flatulence, constipation, mouth ulceration, dysphagia, abdominal distention, pancreatitis, gastrointestinal perforation, eructation, dry mouth

General disorders and administration site conditions: fatigue, injection site inflammation, edema, pain, malaise, asthenia, chest pain, multiple organ failure

Immune system disorders: hypersensitivity

Infections and infestations: candida infections including oral candidiasis, upper respiratory infection, influenza, urinary tract infection, cellulitis

Investigations: blood alkaline phosphatase increased, hepatic function abnormal, aspartate aminotransferase increased, alanine aminotransferase increased, creatinine clearance decreased

Metabolism and nutrition disorders: weight decreased

Musculoskeletal and connective tissue disorders: back pain, myalgia, arthralgia, muscle spasms, leg cramps, myasthenia

Nervous system disorders: headache, insomnia, dizziness, paresthesia, hypoesthesia, seizure, somnolence, dysgeusia (taste disturbance), tremor

Psychiatric disorders: depression, confusional state, anxiety, agitation, psychotic disorder, thinking abnormal, abnormal dreams

Renal and urinary disorders: kidney failure, renal function abnormal, urinary frequency, hematuria

Respiratory, thoracic and mediastinal disorders: cough, dyspnea

Skin and subcutaneous tissues disorders: dermatitis, alopecia, dry skin, urticaria, rash

Vascular disorders: hypotension, hypertension, phlebitis, vasodilation

6.2 Postmarketing Experience

The following adverse reactions have been identified during post-approval use of Ganciclovir for Injection or ganciclovir capsules. Because these reactions are reported voluntarily from a population of uncertain size, it is not always possible to reliably estimate their frequency or establish a causal relationship to drug exposure.

Blood and lymphatic disorders: hemolytic anemia, agranulocytosis, granulocytopenia

Cardiac disorders: cardiac arrest, conduction disorder, torsade de pointes, ventricular tachycardia

Congenital, familial and genetic disorders: congenital anomaly

Endocrine disorders: inappropriate antidiuretic hormone secretion

Eye disorders: cataracts, dry eyes

Gastrointestinal disorders: intestinal ulcer

Hepatobiliary disorders: cholelithiasis, cholestasis, hepatic failure, hepatitis

Immune system disorders: anaphylactic reaction, allergic reaction, vasculitis

Investigations: blood triglycerides increased

Metabolism and nutrition disorders: acidosis, hypercalcemia, hyponatremia

Musculoskeletal and connective tissue disorders: arthritis, rhabdomyolysis

Nervous system disorders: dysesthesia, dysphasia, extrapyramidal disorder, facial paralysis, amnesia, anosmia, myelopathy, cerebrovascular accident, third cranial nerve paralysis, aphasia, encephalopathy, intracranial hypertension

Psychiatric disorders: irritability, hallucinations

Renal and urinary disorders: renal tubular disorder, hemolytic uremic syndrome

Reproductive system and breast disorders: infertility, testicular hypotrophy

Respiratory, thoracic and mediastinal disorders: bronchospasm, pulmonary fibrosis

Skin and subcutaneous tissues disorders: exfoliative dermatitis, Stevens-Johnson syndrome

Vascular disorders: peripheral ischemia

7 DRUG INTERACTIONS

Drug-drug interaction studies were conducted in patients with normal renal function. Patients with impaired renal function may have increased concentrations of ganciclovir and the coadministered drug following concomitant administration of Ganciclovir for Injection and drugs excreted by the same pathway as ganciclovir. Therefore, these patients should be closely monitored for toxicity of ganciclovir and the coadministered drug.

Established and other potentially significant drug interactions conducted with ganciclovir are listed in Table 6 [see Clinical Pharmacology (12.3)].

Table 6. Established and Other Potentially Significant Drug Interactions with Ganciclovir for Injection
Name of the Concomitant Drug | Change in the Concentration of Ganciclovir or Concomitant Drug | Clinical Comment
Imipenem-cilastatin | Unknown | Coadministration with imipenem-cilastatin is not recommended because generalized seizures have been reported in patients who received ganciclovir and imipenem-cilastatin.
Cyclosporine or amphotericin B | Unknown | Monitor renal function when Ganciclovir is coadministered with cyclosporine or amphotericin B because of potential increase in serum creatinine [see Warnings and Precautions (5.2)].
Mycophenolate mofetil (MMF) | ↔ Ganciclovir (in patients with normal renal function) ↔ MMF (in patients with normal renal function) | Based on increased risk, patients should be monitored for hematological and renal toxicity.
Other drugs associated with myelosuppression or nephrotoxicity (e.g., dapsone, doxorubicin, flucytosine, hydroxyurea, pentamidine, tacrolimus, trimethoprim/sulfamethoxazole, vinblastine, vincristine and zidovudine) | Unknown | Because of potential for higher toxicity, coadministration with Ganciclovir should be considered only if the potential benefits are judged to outweigh the risks.
Didanosine | ↔ Ganciclovir ↑ Didanosine | Patients should be closely monitored for didanosine toxicity (e.g., pancreatitis).
Probenecid | ↑Ganciclovir | Ganciclovir for Injection dose may need to be reduced. Monitor for evidence of ganciclovir toxicity.

8 USE IN SPECIFIC POPULATIONS

8.1 Pregnancy

Risk Summary

In animal studies, ganciclovir caused maternal and fetal toxicity and embryo-fetal mortality in pregnant mice and rabbits as well as teratogenicity in rabbits at exposures two times the exposure at the recommended human dose (RHD) [see Data]. Although placental transfer of ganciclovir has been shown to occur based on ex vivo experiments with human placenta and in at least one case report in a pregnant woman, no adequate human data are available to establish whether Ganciclovir for Injection poses a risk to pregnancy outcomes. The background risk of major birth defects and miscarriage for the indicated populations is unknown. In the U.S. general population, the estimated background risk of major birth defects and miscarriage in the clinically recognized pregnancies is 2-4% and 15-20%, respectively.

Clinical Considerations

Disease-associated maternal and/or embryo-fetal risk

Most maternal CMV infections are asymptomatic or they may be associated with a self-limited mononucleosis-like syndrome. However, in immunocompromised patients (i.e., transplant patients or patients with AIDS), CMV infections may be symptomatic and may result in significant maternal morbidity and mortality. The transmission of CMV to the fetus is a result of maternal viremia and transplacental infection. Perinatal infection can also occur from exposure of the neonate to CMV shedding in the genital tract. Approximately 10% of children with congenital CMV infection are symptomatic at birth. Mortality in symptomatic infants is about 10% and approximately 50-90% of symptomatic surviving newborns experience significant morbidity, including mental retardation, sensorineural hearing loss, microcephaly, seizures, and other medical problems. The risk of congenital CMV infection resulting from primary maternal CMV infection may be higher and of greater severity than that resulting from maternal reactivation of CMV infection.

Data

Animal Data

Daily intravenous doses of ganciclovir were administered to pregnant mice (108 mg/kg/day) and rabbits (60 mg/kg/day), and also to female mice (90 mg/kg) prior to mating, during gestation, and during lactation. Fetal resorptions were present in at least 85% of rabbits and mice. Additional effects observed in rabbits included fetal growth retardation, embryolethality, teratogenicity, and/or maternal toxicity. Teratogenic changes included cleft palate, anophthalmia/microphthalmia, aplastic organs (kidney and pancreas), hydrocephaly, and brachygnathia. In pre/postnatal development studies in mice, there were maternal/fetal toxicity and embryolethality which included fetal effects of hypoplasia of the testes and seminal vesicles in the male offspring, as well as pathologic changes in the nonglandular region of the stomach. The systemic exposure (AUC) of ganciclovir during these studies was approximately 2 times (pregnant mice and rabbits) and 1.7 times (pre/postnatal mice) the exposure in humans at the RHD [see Nonclinical Toxicology (13.1)].

8.2 Lactation

Risk Summary

No data are available regarding the presence of ganciclovir in human milk, the effects on the breastfed infant, or the effects on milk production. When ganciclovir was administered to lactating rats, ganciclovir was present in milk [see Data]. Advise nursing mothers that breastfeeding is not recommended during treatment with Ganciclovir because of the potential for serious adverse reactions in nursing infants [see Warnings and Precautions (5.1, 5.3, 5.4, 5.5), Nonclinical Toxicology (13.1)]. Furthermore, the Centers for Disease Control and Prevention recommends that HIV-infected mothers not breastfeed their infants to avoid potential postnatal transmission of HIV.

Data

Animal Data

Ganciclovir administered intravenously (at 0.13 mg/h) to lactating rats (on lactation day 15) resulted in passive transfer into milk. The milk-to-serum ratio for ganciclovir at steady state was 1.6 ± 0.33.

8.3 Females and Males of Reproductive Potential

Pregnancy Testing

Females of reproductive potential should undergo pregnancy testing before initiation of treatment with Ganciclovir [see Dosage and Administration (2.2), Use in Specific Populations (8.1)].

Contraception

Females

Because of the mutagenic and teratogenic potential of Ganciclovir, females of reproductive potential should be advised to use effective contraception during treatment and for at least 30 days following treatment with Ganciclovir [see Dosage and Administration (2.2), Warnings and Precautions (5.4), Nonclinical Toxicology (13.1)].

Males

Because of its mutagenic potential, males should be advised to practice barrier contraception during and for at least 90 days following treatment with Ganciclovir [see Warnings and Precautions (5.4), Nonclinical Toxicology (13.1)].

Infertility

Ganciclovir at the recommended doses may cause temporary or permanent female and male infertility [see Warnings and Precautions (5.3), Nonclinical Toxicology (13.1)].

Data

Human Data

In a small, open-label, non-randomized clinical study, adult male renal transplant patients receiving valganciclovir (the prodrug of ganciclovir) for CMV prophylaxis for up to 200 days post-transplantation were compared to an untreated control group. Patients were followed-up for six months after valganciclovir discontinuation. Among 24 evaluable patients in the valganciclovir group, the mean sperm density at the end of treatment visit decreased by 11 million/mL from baseline; whereas, among 14 evaluable patients in the control group the mean sperm density increased by 33 million/mL. However, at the follow-up visit among 20 evaluable patients in the valganciclovir group, the mean sperm density was comparable to that observed among 10 evaluable patients in the untreated control group (the mean sperm density at the end of follow-up visit increased by 41 million/mL from baseline in the valganciclovir group and by 43 million/mL in the untreated group).

8.4 Pediatric Use

Safety and efficacy of Ganciclovir have not been established in pediatric patients.

A total of 120 pediatric patients with serious CMV infections participated in clinical trials.

Granulocytopenia and thrombocytopenia were the most common adverse reactions. The pharmacokinetic characteristics of ganciclovir after administration of Ganciclovir were studied in 27 neonates (aged 2 to 49 days) and 10 pediatric patients, aged 9 months to 12 years. In neonates, the pharmacokinetic parameters after ganciclovir intravenous doses of 4 mg/kg (n=14) and 6 mg/kg (n=13) were Cmax 5.5 ± 1.6 and 7.0 ± 1.6 mcg/mL, systemic clearance 3.14 ± 1.75 and 3.56 ± 1.27 mL/min/kg, and t1/2 of 2.4 hours (harmonic mean) for both doses, respectively.

In pediatric patients 9 months to 12 years of age, the pharmacokinetic characteristics of ganciclovir were the same after single and multiple (every 12 hours) intravenous doses (5 mg/kg). The steady-state volume of distribution was 0.64 ± 0.22 L/kg, Cmax was 7.9 ± 3.9 mcg/mL, systemic clearance was 4.7 ± 2.2 mL/min/kg, and t1/2 was 2.4 ± 0.7 hours.

Although the pharmacokinetics of Ganciclovir in pediatric patients were similar to those observed in adults, the safety and efficacy of ganciclovir at these exposures in pediatric patients have not been established.

8.5 Geriatric Use

Clinical studies of Ganciclovir did not include sufficient numbers of subjects aged 65 and over to determine whether they respond differently from younger subjects. In general, dose selection for an elderly patient should be cautious, reflecting the greater frequency of decreased hepatic, renal, or cardiac function, and of concomitant disease or other drug therapy. Ganciclovir is known to be substantially excreted by the kidney, and the risk of toxic reactions to this drug may be greater in patients with impaired renal function. Because renal clearance decreases with age, Ganciclovir should be administered to elderly patients with special consideration of their renal status. Renal function should be monitored and dosage adjustments should be made accordingly [see Dosage and Administration (2.5), Warnings and Precautions (5.2), Use in Specific Populations (8.6)].

8.6 Renal Impairment

Dose reduction is recommended when administering Ganciclovir to patients with renal impairment [see Dosage and Administration (2.5), Warnings and Precautions (5.2)].

8.7 Hepatic Impairment

The safety and efficacy of Ganciclovir have not been studied in patients with hepatic impairment.

10 OVERDOSAGE

Reports of adverse reactions after overdoses with Ganciclovir, some with fatal outcomes, have been received from clinical trials and during postmarketing experience. One or more of the following adverse reactions has been reported with overdoses:

Hematological toxicity: myelosuppression including pancytopenia, leukopenia, neutropenia, granulocytopenia, thrombocytopenia, bone marrow failure

Hepatotoxicity: hepatitis, liver function disorder

Renal toxicity: worsening of hematuria in a patient with pre-existing renal impairment, acute kidney injury, elevated creatinine

Gastrointestinal toxicity: abdominal pain, diarrhea, vomiting

Neurotoxicity: seizure

Since ganciclovir is dialyzable, dialysis may be useful in reducing serum concentrations in patients who have received an overdose of Ganciclovir [see Clinical Pharmacology (12.3)]. Adequate hydration should be maintained. The use of hematopoietic growth factors should be considered in patients with cytopenias [see Warnings and Precautions (5.1)].

11 DESCRIPTION

Ganciclovir for Injection, USP contains ganciclovir, in the form of the sodium salt for intravenous injection. Ganciclovir is a synthetic guanine derivative active against cytomegalovirus (CMV).

Chemically, ganciclovir is 9-[[2-hydroxy-1-(hydroxymethyl)-ethoxy]methyl]guanine and ganciclovir sodium is 9-[[2-hydroxy-1-(hydroxymethyl)-ethoxy]methyl]guanine, monosodium salt. The chemical structures of ganciclovir sodium and ganciclovir are:

Ganciclovir is a white to off-white crystalline powder. Ganciclovir is a polar hydrophilic compound with a solubility of 2.6 mg/mL in water at 25°C and an n-octanol/water partition coefficient of 0.022. The pKas for ganciclovir are 2.2 and 9.4.

Ganciclovir for Injection, USP, formulated as monosodium salt, using sodium hydroxide as a salt forming agent, is a sterile white to off-white lyophilized powder. The lyophilized powder has an aqueous solubility of greater than 50 mg/mL at 25°C. At physiological pH, ganciclovir sodium exists as the unionized form with a solubility of approximately 6 mg/mL at 37°C.

Each vial contains 543 mg ganciclovir sodium equivalent to 500 mg ganciclovir.

Inactive ingredients may include hydrochloric acid (QS) and sodium hydroxide (QS) added to adjust the pH.

All doses in this package insert are specified in terms of ganciclovir.

12 CLINICAL PHARMACOLOGY

12.1 Mechanism of Action

Ganciclovir is an antiviral drug with activity against CMV [see Microbiology (12.4)].

12.3 Pharmacokinetics

Absorption

At the end of a 1-hour intravenous infusion of 5 mg/kg ganciclovir, total AUC ranged between 22.1 ± 3.2 (n=16) and 26.8 ± 6.1 mcg·hr/mL (n=16) and Cmax ranged between 8.27 ± 1.02 (n=16) and 9.0 ± 1.4 mcg/mL (n=16).

Distribution

The steady-state volume of distribution of ganciclovir after intravenous administration was 0.74 ± 0.15 L/kg (n=98). Ganciclovir diffuses across the placenta. Cerebrospinal fluid concentrations obtained 0.25 to 5.67 hours post-dose in 3 patients who received 2.5 mg/kg ganciclovir intravenously every 8 hours or every 12 hours ranged from 0.31 to 0.68 mcg/mL, representing 24% to 70% of the respective plasma concentrations. Binding to plasma proteins was 1% to 2% over ganciclovir concentrations of 0.5 and 51 mcg/mL.

Elimination

When administered intravenously, ganciclovir exhibits linear pharmacokinetics over the range of 1.6 to 5.0 mg/kg. Renal excretion of unchanged drug by glomerular filtration and active tubular secretion is the major route of elimination of ganciclovir. In patients with normal renal function, 91.3 ± 5.0% (n=4) of intravenously administered ganciclovir was recovered unmetabolized in the urine. Systemic clearance of intravenously administered ganciclovir was 3.52 ± 0.80 mL/min/kg (n=98) while renal clearance was 3.20 ± 0.80 mL/min/kg (n=47), accounting for 91 ± 11% of the systemic clearance (n=47). Half-life was 3.5 ± 0.9 hours (n=98) following intravenous administration.

Specific Populations

Pharmacokinetics in Patients with Renal Impairment

The pharmacokinetics following intravenous administration of Ganciclovir solution were evaluated in 10 immunocompromised patients with renal impairment who received doses ranging from 1.25 to 5.0 mg/kg. Decreased renal function results in decreased clearance of ganciclovir (Table 7).

Table 7. Ganciclovir Pharmacokinetics in Patients with Renal Impairment
Estimated Creatinine Clearance (mL/min) | n | Dose | Clearance (mL/min) Mean ± SD | Half-life (hours) Mean ± SD
50–79 | 4 | 3.2–5 mg/kg | 128 ± 63 | 4.6 ± 1.4
25–49 | 3 | 3–5 mg/kg | 57 ± 8 | 4.4 ± 0.4
<25 | 3 | 1.25–5 mg/kg | 30 ± 13 | 10.7 ± 5.7

Plasma concentrations of ganciclovir are reduced by about 50% during a 4 hour hemodialysis session.

Pharmacokinetics in Geriatric Patients

The pharmacokinetic profiles of Ganciclovir in patients 65 years of age and older have not been established. As ganciclovir is mainly renally excreted and since renal clearance decreases with age, a decrease in ganciclovir total body clearance and a prolongation of ganciclovir half-life can be anticipated in patients 65 years of age and older [see Dosage and Administration (2.5), Use in Specific Populations (8.5)].

Drug Interaction Studies

Table 8 and Table 9 provide a listing of established drug interaction studies with ganciclovir. Table 8 provides the effects of coadministered drug on ganciclovir plasma pharmacokinetic parameters, whereas Table 9 provides the effects of ganciclovir on plasma pharmacokinetic parameters of coadministered drug.

Table 8. Results of Drug Interaction Studies with Ganciclovir: Effects of Coadministered Drug on Ganciclovir Pharmacokinetic Parameters
Coadministered Drug | Ganciclovir Dosage | N | Ganciclovir Pharmacokinetic (PK) Parameter
Mycophenolate mofetil (MMF) 1.5 g single dose | 5 mg/kg IV single dose | 12 | No effect on ganciclovir PK parameters observed (patients with normal renal function)
Trimethoprim 200 mg once daily | 1000 mg orally every 8 hours | 12 | No effect on ganciclovir PK parameters observed.
Didanosine 200 mg every 12 hours simultaneously administered with ganciclovir | 5 mg/kg IV twice daily | 11 | No effect on ganciclovir PK parameters observed
Didanosine 200 mg every 12 hours simultaneously administered with ganciclovir | 5 mg/kg IV once daily | 11 | No effect on ganciclovir PK parameters observed
Probenecid 500 mg every 6 hours | 1000 mg orally every 8 hours | 10 | AUC ↑ 53 ± 91% (range: -14% to 299%) Ganciclovir renal clearance ↓ 22 ± 20% (range: -54% to -4%)

Table 9. Results of Drug Interaction Studies with Ganciclovir: Effects of Ganciclovir on Pharmacokinetic Parameters of Coadministered Drug Coadministered Drug
Coadministered Drug | Ganciclovir Dosage | N | Coadministered Drug Pharmacokinetic (PK) Parameter
Oral cyclosporine at therapeutic doses | 5 mg/kg infused over 1 hour every 12 hours | 93 | In a retrospective analysis of liver allograft recipients, there was no evidence of an effect on cyclosporine whole blood concentrations.
Mycophenolate mofetil (MMF) 1.5 g single dose | 5 mg/kg IV single dose | 12 | No PK interaction observed (patients with normal renal function)
Trimethoprim 200 mg once daily | 1000 mg orally every 8 hours | 12 | No effect on trimethoprim PK parameters observed.
Didanosine 200 mg every 12 hours | 5 mg/kg IV twice daily | 11 | AUC0-12 ↑70 ± 40% (range: 3% to 121%) Cmax ↑49 ± 48% (range: -28% to 125%)
Didanosine 200 mg every 12 hours | 5 mg/kg IV once daily | 11 | AUC0-12 ↑50 ± 26% (range: 22% to 110%) Cmax ↑36 ± 36% (range: -27% to 94%)

12.4 Microbiology

Mechanism of Action

Ganciclovir is a synthetic analogue of 2'-deoxyguanosine, which inhibits replication of human CMV in cell culture and in vivo. In CMV-infected cells, ganciclovir is initially phosphorylated to ganciclovir monophosphate by the viral protein kinase, pUL97. Further phosphorylation occurs by cellular kinases to produce ganciclovir triphosphate, which is then slowly metabolized intracellularly. As the phosphorylation is largely dependent on the viral kinase, phosphorylation of ganciclovir occurs preferentially in virus-infected cells. The virustatic activity of ganciclovir is due to inhibition of the viral DNA polymerase, pUL54, by ganciclovir triphosphate.

Antiviral Activity

The quantitative relationship between the cell culture susceptibility of human herpes viruses to antivirals and clinical response to antiviral therapy has not been established, and virus sensitivity testing has not been standardized. Sensitivity test results, expressed as the concentration of drug required to inhibit the growth of virus in cell culture by 50% (EC50), vary greatly depending upon a number of factors including the assay used. Thus the median concentration of ganciclovir that inhibits CMV replication (EC50 value) in cell culture (laboratory strains or clinical isolates) has ranged from 0.08 to 13.6 μM (0.02 to 3.48 mcg/mL). Ganciclovir inhibits mammalian cell proliferation (CC50 value) in cell culture at higher concentrations ranging from 118 to 2840 μM (30 to 725 mcg/mL). Bone marrow-derived colony-forming cells are more sensitive [CC50 value = 0.1 to 2.7 μM (0.028 to 0.7 mcg/mL)]. The relationship between the antiviral activity in cell culture and clinical response has not been established.

Viral Resistance

Cell Culture: CMV isolates with reduced susceptibility to ganciclovir have been selected in cell culture. Growth of CMV strains in the presence of ganciclovir resulted in the selection of amino acid substitutions in the viral protein kinase pUL97 and the viral DNA polymerase pUL54.

In vivo: Viruses resistant to ganciclovir can arise after prolonged treatment or prophylaxis with ganciclovir by selection of substitutions in pUL97 and/or pUL54. Limited clinical data are available on the development of clinical resistance to ganciclovir and many pathways to resistance likely exist. In clinical isolates, seven canonical pUL97 substitutions, (M460V/I, H520Q, C592G, A594V, L595S, C603W) are the most frequently reported ganciclovir resistance-associated substitutions. These and other substitutions less frequently reported in the literature, or observed in clinical trials, are listed in Table 10.

Table 10. Summary of Resistance-associated Amino Acid Substitutions Observed in the CMV of Patients Failing Ganciclovir Treatment or Prophylaxis
pUL97 | L405P, A440V, M460I/V/T/L, V466G/M, C518Y, H520Q, P521L, del 590-593, A591D/V, C592G, A594E/G/T/V/P, L595F/S/T/W, del 595, del 595-603, E596D/G/Y, K599E/M, del 600-601, del 597-600, del 601-603, C603W/R/S/Y, C607F/S/Y, I610T, A613V
pUL54 | E315D, N408D/K/S, F412C/L/S, D413A/E/N, L501F/I, T503I, K513E/N/R, D515E, L516W, I521T, P522A/L/S, V526L, C539G, L545S/W, Q578H/L, D588E/N, G629S, S695T, I726T/V, E756K, L773V, V781I, V787L, L802M, A809V, T813S, T821I, A834P, G841A/S, D879G, A972V, del 981-982, A987G

Note: Many additional pathways to ganciclovir resistance likely exist.

CMV resistance to ganciclovir has been observed in individuals with AIDS and CMV retinitis who have never received ganciclovir therapy. Viral resistance has also been observed in patients receiving prolonged treatment for CMV retinitis with Ganciclovir. In a controlled study of oral ganciclovir for prevention of AIDS-associated CMV disease, 364 individuals had one or more cultures performed after at least 90 days of ganciclovir treatment. Of these, 113 had at least one positive culture. The last available isolate from each subject was tested for reduced sensitivity, and 2 of 40 were found to be resistant to ganciclovir. These resistant isolates were associated with subsequent treatment failure for retinitis.

The possibility of viral resistance should be considered in patients who show poor clinical response or experience persistent viral excretion during therapy.

Cross-Resistance

Cross-resistance has been reported for amino acid substitutions selected in cell culture by ganciclovir, cidofovir or foscarnet. In general, amino acid substitutions in pUL54 conferring cross-resistance to ganciclovir and cidofovir are located within the exonuclease domains and region V of the viral DNA polymerase. Whereas, amino acid substitutions conferring cross-resistance to foscarnet are diverse, but concentrate at and between regions II (codons 696-742) and III (codons 805-845). The amino acid substitutions that resulted in reduced susceptibility to ganciclovir and either cidofovir and/or foscarnet are summarized in Table 11.

Table 11. Summary of pUL54 Amino Acid Substitutions with Cross-resistance between Ganciclovir, Cidofovir, and/or Foscarnet
Cross-resistant to cidofovir | D301N, N408D/K, N410K, F412C/L/S/V, D413E/N, P488R, L501I, T503I, K513E/N, L516R/W, I521T, P522S/A, V526L, C539G/R, L545S/W, Q578H, D588N, I726T/V, E756K, L773V, V812L, T813S, A834P, G841A, del 981-982, A987G
Cross-resistant to foscarnet | F412C, Q578H/L, D588N, V715A/M, E756K, L773V, V781I, V787L, L802M, A809V, V812L, T813S, T821I, A834P, G841A/S, del 981-982

13 NONCLINICAL TOXICOLOGY

13.1 Carcinogenesis, Mutagenesis, Impairment of Fertility

Carcinogenesis, Mutagenesis

Ganciclovir was carcinogenic in mice at the same mean drug exposure in humans as at the RHD (5 mg/kg). At the dose of 1000 mg/kg/day (1.4 times the exposure at the RHD), there was a significant increase in the incidence of tumors of the preputial gland in males, forestomach (nonglandular mucosa) in males and females, and reproductive tissues (ovaries, uterus, mammary gland, clitoral gland and vagina) and liver in females. At the dose of 20 mg/kg/day (0.1 times the exposure at the RHD), a slightly increased incidence of tumors was noted in the preputial and harderian glands in males, forestomach in males and females, and liver in females. No carcinogenic effect was observed in mice administered ganciclovir at 1 mg/kg/day (exposure estimated as 0.01 times the RHD). Except for histiocytic sarcoma of the liver, ganciclovir-induced tumors were generally of epithelial or vascular origin. Although the preputial and clitoral glands, forestomach and harderian glands of mice do not have human counterparts, ganciclovir should be considered a potential carcinogen in humans.

Ganciclovir increased mutations in mouse lymphoma cells and DNA damage in human lymphocytes in vitro at concentrations between 50 to 500 and 250 to 2000 μg/mL, respectively. In the mouse micro nucleus assay, ganciclovir was clastogenic at doses of 150 and 500 mg/kg (2.8 to 10 times the exposure at the RHD) but not at doses of 50 mg/kg (exposure approximately comparable to the RHD). Ganciclovir was not mutagenic in the Ames Salmonella assay at concentrations of 500 to 5000 μg/mL.

Impairment of Fertility

Ganciclovir caused decreased mating behavior, decreased fertility, and an increased incidence of embryolethality in female mice following doses of 90 mg/kg/day (exposures approximately 1.7 times the RHD). Ganciclovir caused decreased fertility in male mice and hypospermatogenesis in mice and dogs following daily oral or intravenous administration of doses ranging from 0.2 to 10 mg/kg. Systemic drug exposure (AUC) at the lowest dose showing toxicity in each species ranged from 0.03 to 0.1 times the exposure at the RHD.

14 CLINICAL STUDIES

14.1 Treatment of CMV Retinitis

In a retrospective, non-randomized, single-center analysis of 41 patients with AIDS and CMV retinitis diagnosed by ophthalmologic examination between August 1983 and April 1988, treatment with Ganciclovir solution resulted in a delay in mean (median) time to first retinitis progression compared to untreated controls [105 (71) days from diagnosis vs 35 (29) days from diagnosis]. Patients in this series received induction treatment of Ganciclovir 5 mg/kg twice daily for 14 to 21 days followed by maintenance treatment with either 5 mg/kg once daily, 7 days per week or 6 mg/kg once daily, 5 days per week.

In a controlled, randomized study conducted between February 1989 and December 1990, immediate treatment with Ganciclovir was compared to delayed treatment in 42 patients with AIDS and peripheral CMV retinitis; 35 of 42 patients (13 in the immediate-treatment group and 22 in the delayed-treatment group) were included in the analysis of time to retinitis progression. Based on masked assessment of fundus photographs, the mean [95% CI] and median [95% CI] times to progression of retinitis were 66 days [39, 94] and 50 days [40, 84], respectively, in the immediate-treatment group compared to 19 days [11, 27] and 13.5 days [8, 18], respectively, in the delayed-treatment group.

Data from trials ICM 1653, ICM 1774, and AVI 034, which were performed comparing Ganciclovir for injection to oral ganciclovir for treatment of CMV retinitis in patients with AIDS, are shown in Table 12 and Figures 1, 2, and 3, and are discussed below.

Table 12. Population Characteristics in Studies ICM 1653, ICM 1774 and AVI 034
Demographics |  | ICM 1653 (n=121) | ICM 1774 (n=225) | AVI 034 (n=159)
Median age (years) Range |  | 38 24–62 | 37 22–56 | 39 23–62
Sex | Males | 116 (96%) | 222 (99%) | 148 (93%)
Sex | Females | 5 (4%) | 3 (1%) | 10 (6%)
Ethnicity | Asian | 3 (3%) | 5 (2%) | 7 (4%)
Ethnicity | Black | 11 (9%) | 9 (4%) | 3 (2%)
Ethnicity | Caucasian | 98 (81%) | 186 (83%) | 140 (88%)
Ethnicity | Other | 9 (7%) | 25 (11%) | 8 (5%)
Median CD4 Count Range |  | 9.5 0-141 | 7.0 0-80 | 10.0 0-320
Mean (SD) Observation Time (days) |  | 107.9 (43.0) | 97.6 (42.5) | 80.9 (47.0)

Trial ICM 1653: In this randomized, open-label, parallel group trial, conducted between March 1991 and November 1992, patients with AIDS and newly diagnosed CMV retinitis received a 3-week induction course of Ganciclovir solution, 5 mg/kg twice daily for 14 days followed by 5 mg/kg once daily for 1 additional week. Following the 21-day intravenous induction course, patients with stable CMV retinitis were randomized to receive 20 weeks of maintenance treatment with either Ganciclovir solution, 5 mg/kg once daily, or ganciclovir capsules, 500 mg 6 times daily (3000 mg/day). The study showed that the mean [95% CI] and median [95% CI] times to progression of CMV retinitis, as assessed by masked reading of fundus photographs, were 57 days [44, 70] and 29 days [28, 43], respectively, for patients on oral therapy compared to 62 days [50, 73] and 49 days [29, 61], respectively, for patients on intravenous therapy. The difference [95% CI] in the mean time to progression between the oral and intravenous therapies (oral - IV) was -5 days [-22, 12]. See Figure 1 for comparison of the proportion of patients remaining free of progression over time.

Trial ICM 1774: In this three-arm, randomized, open-label, parallel group trial, conducted between June 1991 and August 1993, patients with AIDS and stable CMV retinitis following from 4 weeks to 4 months of treatment with Ganciclovir solution were randomized to receive maintenance treatment with Ganciclovir solution, 5 mg/kg once daily, ganciclovir capsules, 500 mg 6 times daily, or ganciclovir capsules, 1000 mg three times daily for 20 weeks. The study showed that the mean [95% CI] and median [95% CI] times to progression of CMV retinitis, as assessed by masked reading of fundus photographs, were 54 days [48, 60] and 42 days [31, 54], respectively, for patients on oral therapy compared to 66 days [56, 76] and 54 days [41, 69], respectively, for patients on intravenous therapy. The difference [95% CI] in the mean time to progression between the oral and intravenous therapies (oral - IV) was -12 days [-24, 0]. See Figure 2 for comparison of the proportion of patients remaining free of progression over time.

Trial AVI 034: In this randomized, open-label, parallel group trial, conducted between June 1991 and February 1993, patients with AIDS and newly diagnosed (81%) or previously treated (19%) CMV retinitis who had tolerated 10 to 21 days of induction treatment with Ganciclovir, 5 mg/kg twice daily, were randomized to receive 20 weeks of maintenance treatment with either ganciclovir capsules, 500 mg 6 times daily, or Ganciclovir solution, 5 mg/kg/day. The mean [95% CI] and median [95% CI] times to progression of CMV retinitis, as assessed by masked reading of fundus photographs, were 51 days [44, 57] and 41 days [31, 45], respectively, for patients on oral therapy compared to 62 days [52, 72] and 60 days [42, 83], respectively, for patients on intravenous therapy. The difference [95% CI] in the mean time to progression between the oral and intravenous therapies (oral - IV) was -11 days [-24, 1]. See Figure 3 for comparison of the proportion of patients remaining free of progression over time.

Comparison of other CMV retinitis outcomes between oral and IV formulations (development of bilateral retinitis, progression into Zone 1, and deterioration of visual acuity), while not definitive, showed no marked differences between treatment groups in these studies. Because of low event rates among these endpoints, these studies are underpowered to rule out significant differences in these endpoints.

Figure 1 Trial ICM 1653: Time to Progression of CMV Retinitis

Figure 2 Trial ICM 1774: Time to Progression of CMV Retinitis

Figure 3 Trial AVI 034: Time to Progression of Retinitis

14.2 Prevention of CMV Disease in Transplant Recipients

Ganciclovir was evaluated in three randomized, controlled trials of prevention of CMV disease in organ transplant recipients.

Trial ICM 1496: In a randomized, double-blind, placebo-controlled study of 149 heart transplant recipients at risk for CMV infection (CMV seropositive or a seronegative recipient of an organ from a CMV seropositive donor), there was a reduction in the overall incidence of CMV disease in patients treated with Ganciclovir. Immediately post-transplant, patients received Ganciclovir solution 5 mg/kg twice daily for 14 days followed by 6 mg/kg once daily for 5 days/week for an additional 14 days. Twelve of the 76 (16%) patients treated with Ganciclovir vs 31 of the 73 (43%) placebo-treated patients developed CMV disease during the 120-day post-transplant observation period. No significant differences in hematologic toxicities were seen between the two treatment groups [see Adverse Reactions (6.1)].

Trial ICM 1689: In a randomized, double-blind, placebo-controlled study of 72 bone marrow transplant recipients with asymptomatic CMV infection (CMV positive culture of urine, throat or blood) there was a reduction in the incidence of CMV disease in patients treated with Ganciclovir following successful hematopoietic engraftment. Patients with virologic evidence of CMV infection received Ganciclovir solution 5 mg/kg twice daily for 7 days followed by 5 mg/kg once daily through day 100 post-transplant. One of the 37 (3%) patients treated with Ganciclovir vs 15 of the 35 (43%) placebo-treated patients developed CMV disease during the study. At 6 months post-transplant, there continued to be a reduction in the incidence of CMV disease in patients treated with Ganciclovir. Six of 37 (16%) patients treated with Ganciclovir vs 15 of the 35 (43%) placebo-treated patients developed disease through 6 months post-transplant. The overall rate of survival was higher in the group treated with Ganciclovir, both at day 100 and day 180 post-transplant. Although the differences in hematologic toxicities were not statistically significant, the incidence of neutropenia was higher in the group treated with Ganciclovir [see Adverse Reactions (6.1)].

Trial ICM 1570: This was a randomized, unblinded study that evaluated 40 allogeneic bone marrow transplant recipients at risk for CMV disease. Patients underwent bronchoscopy and bronchoalveolar lavage (BAL) on day 35 post-transplant. Patients with histologic, immunologic or virologic evidence of CMV infection in the lung were then randomized to observation or treatment with Ganciclovir solution (5 mg/kg twice daily for 14 days followed by 5 mg/kg once daily 5 days/week until day 120).

Four of 20 (20%) patients treated with Ganciclovir and 14 of 20 (70%) control patients developed interstitial pneumonia. The incidence of CMV disease was lower in the group treated with Ganciclovir, consistent with the results observed in ICM 1689.

15 REFERENCES

1. "OSHA Hazardous Drugs." OSHA. http://www.osha.gov/SLTC/hazardousdrugs/index.html.

16 HOW SUPPLIED/STORAGE AND HANDLING

Ganciclovir for Injection, USP is supplied as follows:

Product Code | Unit of Sale | Strength | Each
PRX315110 | NDC 63323-315-94 Unit of 25 vials | 500 mg per vial | NDC 63323-315-41 10 mL vial

Because ganciclovir shares some of the properties of antitumor agents (i.e., carcinogenicity and mutagenicity), consideration should be given to handling and disposal according to guidelines issued for antineoplastic drugs.

The container closure is not made with natural rubber latex.

Storage

Store vials at 20° to 25°C (68° to 77°F) [see USP Controlled Room Temperature].

Store reconstituted solution in the vial at 25°C (77°F) for no longer than 12 hours. Do not refrigerate or freeze. Discard any unused portion of the reconstituted solution.

Store diluted infusion solution under refrigeration at 2° to 8°C (36° to 46°F) for no longer than 24 hours. Do not freeze.

17 PATIENT COUNSELING INFORMATION

Hematologic Toxicity

Inform patients that Ganciclovir may cause hematologic toxicity, including granulocytopenia (neutropenia), anemia, and thrombocytopenia. Inform patients that their blood counts and platelet counts should be closely monitored while on treatment [see Warnings and Precautions (5.1)].

Impairment of Renal Function

Inform patients that Ganciclovir has been associated with decreased renal function and that serum creatinine or creatinine clearance should be monitored while on treatment to allow for dosage adjustment in patients with renal impairment [see Warnings and Precautions (5.2)].

Impairment of Fertility

Inform patients that Ganciclovir may cause temporary or permanent infertility in humans [see Warnings and Precautions (5.3), Use in Specific Populations (8.3)].

Pregnancy and Contraception

Advise female patients to use effective contraception during and for at least 30 days following treatment with Ganciclovir. Similarly, advise men to practice barrier contraception during and for at least 90 days following treatment with Ganciclovir [see Warnings and Precautions (5.4), Use in Specific Populations (8.1, 8.3)].

Carcinogenicity

Inform patients that Ganciclovir should be considered a potential carcinogen [see Warnings and Precautions (5.5)].

Drug Interactions

Inform patients that Ganciclovir may interact with other drugs. Advise patients to report to their healthcare provider the use of any other medication [see Drug Interactions (7)].

Impairment of Cognitive Ability

Based on the adverse reaction profile, ganciclovir may affect cognitive abilities, including the ability to drive and operate machinery, as seizures, dizziness, and/or confusion have been reported with the use of Ganciclovir [see Adverse Reaction (6.1)].

Ophthalmological Examination in Patients with CMV Retinitis

Inform patients that Ganciclovir is not a cure for CMV retinitis, and they may continue to experience progression of retinitis during or following treatment. Advise patients to have frequent ophthalmological follow-up examinations while being treated with Ganciclovir. Some patients may require more frequent ophthalmological follow-up [see Dosage and Administration (2.2), Adverse Reactions (6.1)].

Lactation

Advise nursing mothers not to breastfeed if they are receiving Ganciclovir because of the potential for serious adverse events in nursing infants and because HIV can be passed to the baby in breast milk [see Use in Specific Populations (8.2)].

PREMIERProRx® is a registered trademark of Premier Healthcare Alliance, L.P., used under license.

Manufactured by:
Fresenius Kabi
Lake Zurich, IL 60047

www.fresenius-kabi.com/us

451373B

PACKAGE LABEL

PACKAGE LABEL - PRINCIPAL DISPLAY - Ganciclovir 500 mg Vial Label

NDC 63323-315-41 PRX315110

GANCICLOVIR

FOR INJECTION, USP

500 mg* per vial

For IV Infusion Only

Handle this drug product with great care because it is a potent cytotoxic agent and suspected carcinogen. Rx only

PACKAGE LABEL

PACKAGE LABEL - PRINCIPAL DISPLAY - Ganciclovir 500 mg Tray Label

NDC 63323-315-94 PRX315110

GANCICLOVIR

FOR INJECTION, USP

500 mg* per vial

For IV Infusion Only

Handle this drug product with great care because it is a potent cytotoxic agent and suspected carcinogen.

25 x 10 mL Vials

Rx only